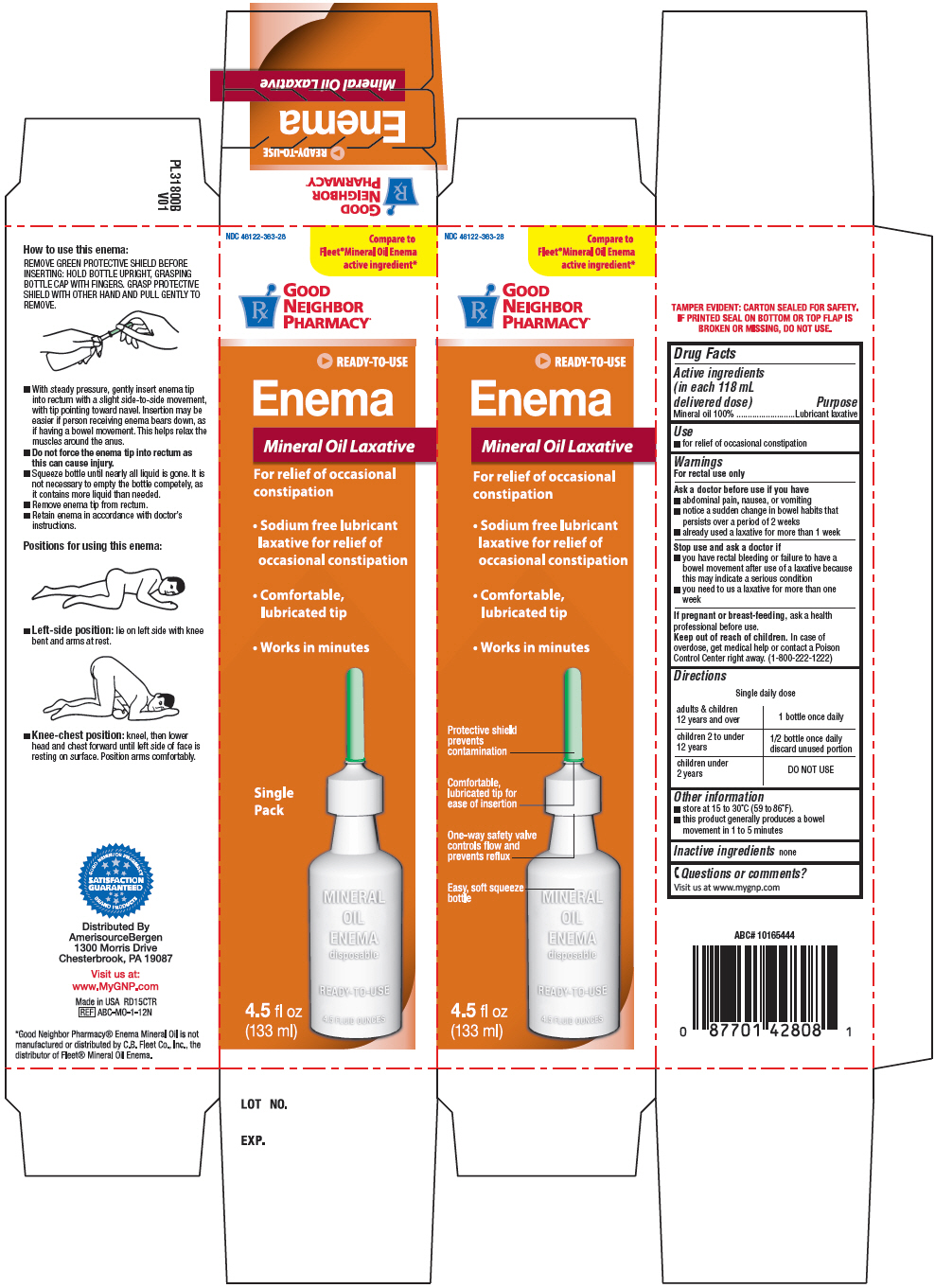 DRUG LABEL: Good Neighbor Pharmacy Mineral Oil Laxative
NDC: 46122-363 | Form: ENEMA
Manufacturer: AmerisourceBergen
Category: otc | Type: HUMAN OTC DRUG LABEL
Date: 20201207

ACTIVE INGREDIENTS: MINERAL OIL 118 g/118 mL

Good Neighbor Pharmacy® Single Saline Laxative
Laxative

Drug Facts

Active ingredients (in each 118 mL delivered dose)

Mineral oil 100%

Purpose

Lubricant laxative

Use

- for relief of occasional constipation

Warnings

For rectal use only

Ask a doctor before use if you have

- abdominal pain, nausea, or vomiting
- notice a sudden change in bowel habits that persists over a period of 2 weeks
- already used a laxative for more than 1 week

Stop use and ask a doctor if

- you have rectal bleeding or failure to have a bowel movement after use of a laxative because this may indicate a serious condition
- you need to us a laxative for more than one week

PREGNANCY OR BREAST FEEDING

If pregnant or breast-feeding, ask a health professional before use.

Keep out of reach of children. In case of overdose, get medical help or contact a Poison Control Center right away. (1-800-222-1222)

Directions

Single daily dose
adults & children 12 years and over | 1 bottle once daily
children 2 to under 12 years | 1/2 bottle once daily discard unused portion
children under 2 years | DO NOT USE

Other information

- store at 15 to 30°C (59 to 86°F).
- this product generally produces a bowel movement in 1 to 5 minutes

Inactive ingredients

none

Questions or comments?

Visit us at www.mygnp.com

Distributed By
AmerisourceBergen
1300 Morris Drive
Chesterbrook, PA 19087

PRINCIPAL DISPLAY PANEL - 133 ml Bottle Carton

NDC 46122-363-28

Compare to
Fleet®Mineral Oil Enema
active ingredient*

GOOD
NEIGHBOR
PHARMACY®

READY-TO-USE

Enema

Mineral Oil Laxative

For relief of occasional
constipation

- Sodium free lubricant
  laxative for relief of
  occasional constipation
- Comfortable,
  lubricated tip
- Works in minutes

Single
Pack

4.5 fl oz
(133 ml)